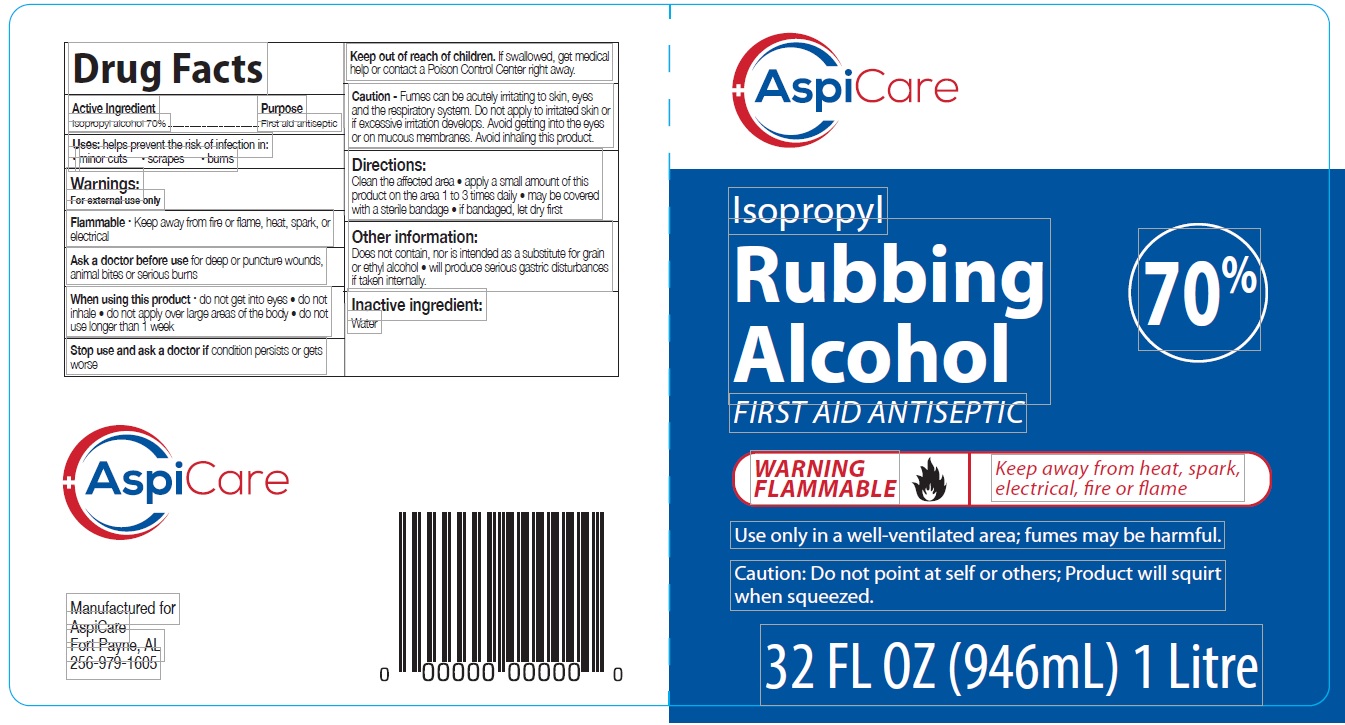 DRUG LABEL: AspiCare
NDC: 70735-072 | Form: SOLUTION
Manufacturer: American Private Label Products
Category: otc | Type: HUMAN OTC DRUG LABEL
Date: 20210308

ACTIVE INGREDIENTS: ISOPROPYL ALCOHOL 70 mL/100 mL
INACTIVE INGREDIENTS: WATER

AspiCare Isopropyl Rubbing Alcohol

Active Ingredient

Isopropyl Alcohol 70% v/v.

Purpose

First Aid Antiseptic

Use

helps prevent the risk of infection in:

- minor cuts
- scrapes
- burns

Warnings

For external use only.

Flammable • Keep away from fire or flame, heat, spark, or electrical

Ask a doctor before use

or deep or puncture wounds, animal bites or serious burns

When using this product

do not get into eyes • do not inhale • do not apply over large areas of the body • do not use longer than 1 week

Stop use and ask a doctor if

condition persists or gets worse

Keep out of reach of children

f swallowed, get medical help or contact a Poison Control Center right away.

Caution

Fumes can be acutely irritating to skin, eyes and the respiratory system. Do not apply to irritated skin or if excessive irritation develops. Avoid getting into the eyes or on mucous membranes. Avoid inhaling this product.

Directions

Clean the affected area • apply a small amount of this product on the area 1 to 3 times daily • may be covered with a sterile bandage • if bandaged, let dry first

Storage

- Store below 110°F (43°C)
- May discolor certain fabrics or surfaces

Inactive ingredients

Water (Aqua)

Other Information

Does not contain, nor is intended as a substitute for grain or ethyl alcohol • will produce serious gastric disturbances if taken internally.

Principal Display Panel

NDC 70735-072-08, 70735-072-16, 70735-072-32, 70735-072-28

Isopropyl Rubbing Alcohol 70%

FIRST AID ANTISEPTIC

WARNING FLAMMABLE

Keep away from heat, spark, electrical, fire or flame

Use only in a well-ventilated area; fumes may be harmful.

Caution: Do not point at self or others; Product will squirt when squeezed.

8 FL OZ (236 mL)

16 FL OZ (473 mL)

32 FL OZ (946 mL) 1 Litre

128 FL OZ (3785 mL)